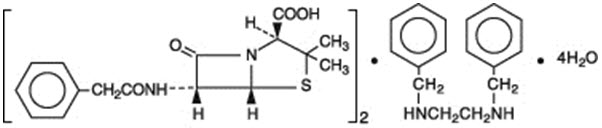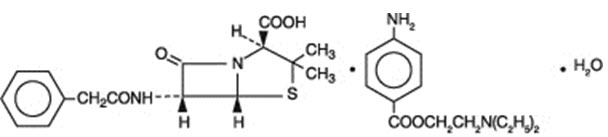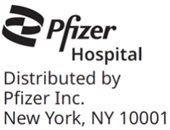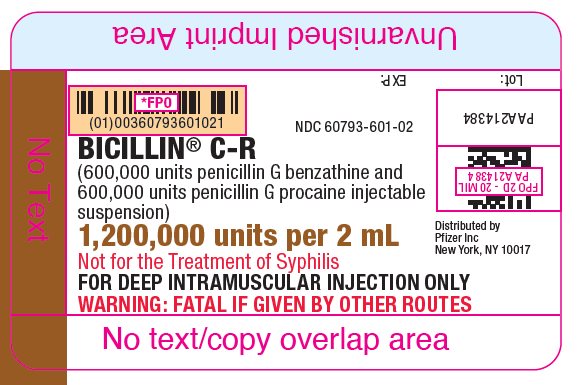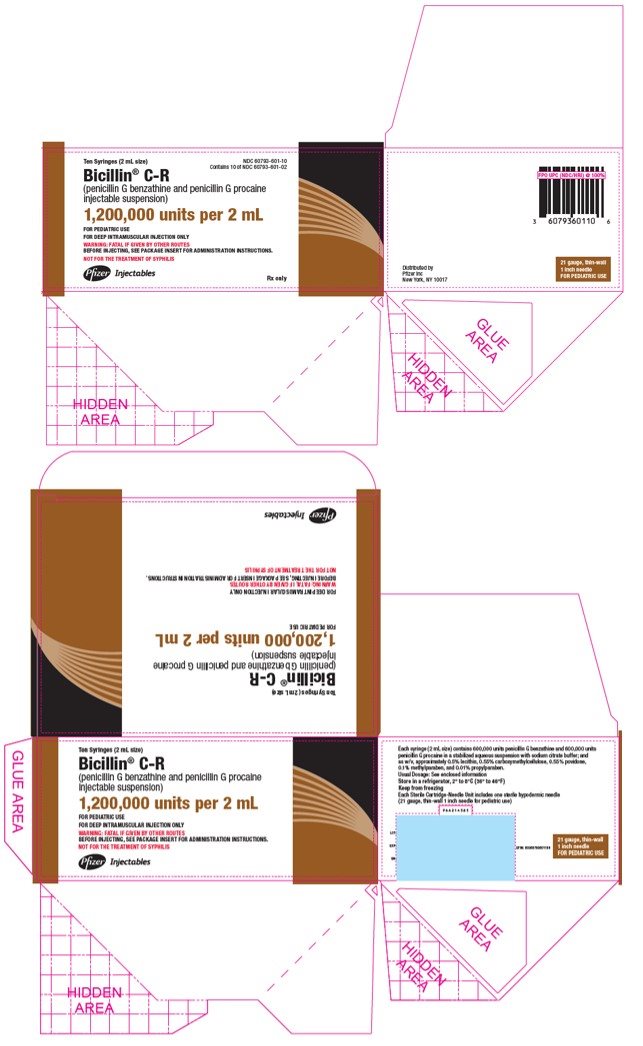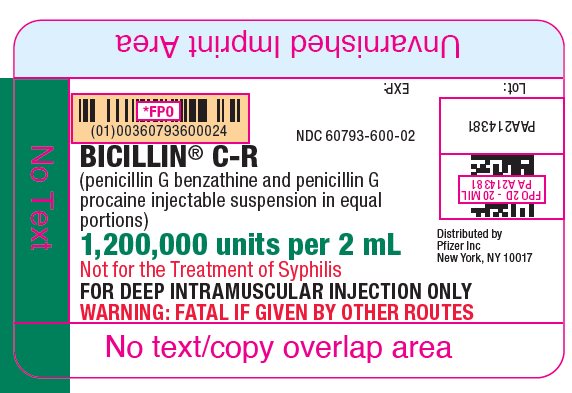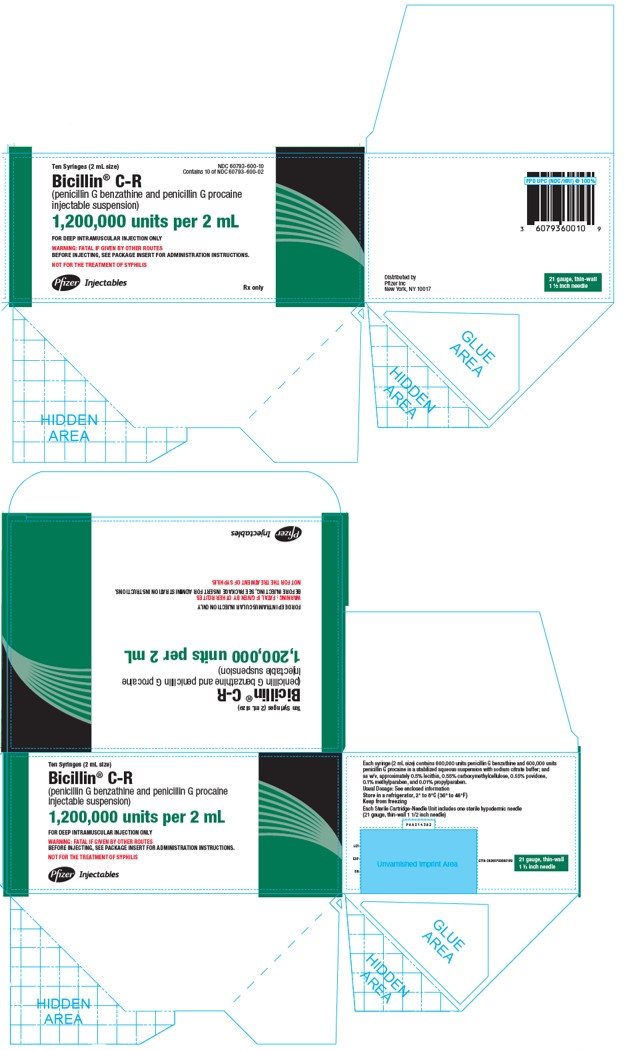 DRUG LABEL: BICILLIN CR
NDC: 60793-601 | Form: INJECTION, SUSPENSION
Manufacturer: Pfizer Laboratories Div Pfizer Inc
Category: prescription | Type: HUMAN PRESCRIPTION DRUG LABEL
Date: 20240604

ACTIVE INGREDIENTS: PENICILLIN G BENZATHINE 600000 [iU]/2 mL; PENICILLIN G PROCAINE 600000 [iU]/2 mL
INACTIVE INGREDIENTS: LECITHIN, SOYBEAN; CARBOXYMETHYLCELLULOSE; POVIDONE, UNSPECIFIED; METHYLPARABEN; PROPYLPARABEN; SODIUM CITRATE, UNSPECIFIED FORM; WATER

Bicillin® C-R
(penicillin G benzathine and penicillin G procaine injectable suspension)
Disposable Syringe
for deep IM injection only

BOXED WARNING

WARNING: NOT FOR INTRAVENOUS USE. DO NOT INJECT INTRAVENOUSLY OR ADMIX WITH OTHER INTRAVENOUS SOLUTIONS. THERE HAVE BEEN REPORTS OF INADVERTENT INTRAVENOUS ADMINISTRATION OF PENICILLIN G BENZATHINE WHICH HAS BEEN ASSOCIATED WITH CARDIORESPIRATORY ARREST AND DEATH. Prior to administration of this drug, carefully read the WARNINGS, ADVERSE REACTIONS, and DOSAGE AND ADMINISTRATIONsections of the labeling.

To reduce the development of drug-resistant bacteria and maintain the effectiveness of Bicillin C-R and other antibacterial drugs, Bicillin C-R should be used only to treat or prevent infections that are proven or strongly suspected to be caused by bacteria.

DESCRIPTION

Bicillin C-R (penicillin G benzathine and penicillin G procaine injectable suspension) contains equal amounts of the benzathine and procaine salts of penicillin G. It is available for deep intramuscular injection.

Penicillin G benzathine is prepared by the reaction of dibenzylethylene diamine with two molecules of penicillin G. It is chemically designated as (2S,5R,6R)-3,3-Dimethyl-7-oxo-6-(2-phenylacetamido)-4-thia-1-azabicyclo[3.2.0]heptane-2-carboxylic acid compound with N,N'-dibenzylethylenediamine (2:1), tetrahydrate. It occurs as a white, crystalline powder and is very slightly soluble in water and sparingly soluble in alcohol. Its chemical structure is as follows:

Molecular Formula
(C16H18N2O4S)2 ∙ C16H20N2 ∙ 4H2O

Molecular Wt.
981.19

Penicillin G procaine, (2S,5R,6R)-3,3-Dimethyl-7-oxo-6-(2-phenylacetamido)-4-thia-1-azabicyclo[3.2.0]heptane-2-carboxylic acid compound with 2-(diethylamino)ethyl p-aminobenzoate (1:1) monohydrate, is an equimolar salt of procaine and penicillin G. It occurs as white crystals or a white, microcrystalline powder and is slightly soluble in water. Its chemical structure is as follows:

Molecular Formula
C16H18N2O4S ∙ C13H20N2O2 ∙ H2O

Molecular Wt.
588.72

Each disposable syringe (2 mL size) contains the equivalent of 1,200,000 units of penicillin G comprising: the equivalent of 600,000 units of penicillin G as the benzathine salt and the equivalent of 600,000 units of penicillin G as the procaine salt in a stabilized aqueous suspension with sodium citrate buffer; and as w/v, approximately 0.5% lecithin, 0.55% carboxymethylcellulose, 0.55% povidone, 0.1% methylparaben, and 0.01% propylparaben.

Bicillin C-R injectable suspension in the disposable-syringe formulation is viscous and opaque. Read CONTRAINDICATIONS, WARNINGS, PRECAUTIONS, and DOSAGE AND ADMINISTRATION sections prior to use.

CLINICAL PHARMACOLOGY

General

Penicillin G benzathine and penicillin G procaine have a low solubility and, thus, the drugs are slowly released from intramuscular injection sites. The drugs are hydrolyzed to penicillin G. This combination of hydrolysis and slow absorption results in blood serum levels much lower but more prolonged than other parenteral penicillins.

Intramuscular administration of 600,000 units of Bicillin C-R in adults usually produces peak blood levels of 1.0 to 1.3 units per mL within 3 hours; this level falls to an average concentration of 0.32 units per mL at 12 hours, 0.19 units per mL at 24 hours, and 0.03 units per mL at seven days.

Intramuscular administration of 1,200,000 units of Bicillin C-R in adults usually produces peak blood levels of 2.1 to 2.6 units per mL within 3 hours; this level falls to an average concentration of 0.75 units per mL at 12 hours, 0.28 units per mL at 24 hours, and 0.04 units per mL at seven days.

Approximately 60% of penicillin G is bound to serum protein. The drug is distributed throughout the body tissues in widely varying amounts. Highest levels are found in the kidneys with lesser amounts in the liver, skin, and intestines. Penicillin G penetrates into all other tissues and the spinal fluid to a lesser degree. With normal kidney function, the drug is excreted rapidly by tubular excretion. In neonates and young infants and in individuals with impaired kidney function, excretion is considerably delayed.

Microbiology

Mechanism of Action

Penicillin G exerts a bactericidal action against penicillin-susceptible microorganisms during the stage of active multiplication. It acts through the inhibition of biosynthesis of cell-wall peptidoglycan, rendering the cell wall osmotically unstable resulting in death of the bacterium.

Resistance

Penicillin is not active against penicillinase-producing bacteria, or against organisms resistant to beta-lactams because of alterations in the penicillin-binding proteins. Resistance to penicillin G has not been reported in Streptococcus pyogenes.

Penicillin has been shown to be active against most isolates of the following bacteria, both in vitro and in clinical infections as described in the INDICATIONS AND USAGE section.

Gram-positive bacteria

Beta-hemolytic streptococci (groups A, B, C, G, H, L and M).

Streptococcus pneumoniae (penicillin-susceptible isolates only).

Susceptibility Testing

For specific information regarding susceptibility test interpretive criteria and associated test methods and quality control standards recognized by FDA for this drug, please see: https://www.fda.gov/STIC.

INDICATIONS AND USAGE

To reduce the development of drug-resistant bacteria and maintain the effectiveness of Bicillin C-R and other antibacterial drugs, Bicillin C-R should be used only to treat or prevent infections that are proven or strongly suspected to be caused by bacteria. When culture and susceptibility information are available, they should be considered in selecting or modifying antibacterial therapy. In the absence of such data, local epidemiology and susceptibility patterns may contribute to the empiric selection of therapy.

This drug is indicated in the treatment of moderately severe infections due to penicillin-G-susceptible microorganisms that are susceptible to serum levels common to this particular dosage form. Therapy should be guided by bacteriological studies (including susceptibility testing) and by clinical response.

Bicillin C-R is indicated in the treatment of the following in adults and pediatric patients:

Moderately severe to severe infections of the upper-respiratory tract, scarlet fever, erysipelas, and skin and soft-tissue infections due to susceptible streptococci.

NOTE: Streptococci in Groups A, C, G, H, L, and M are very sensitive to penicillin G. Other groups, including Group D (enterococci), are resistant. Penicillin G sodium or potassium is recommended for streptococcal infections with bacteremia.

Moderately severe pneumonia and otitis media due to susceptible Streptococcus pneumoniae.

NOTE: Severe pneumonia, empyema, bacteremia, pericarditis, meningitis, peritonitis, and arthritis of pneumococcal etiology are better treated with penicillin G sodium or potassium during the acute stage.

When high, sustained serum levels are required, penicillin G sodium or potassium, either IM or IV, should be used. This drug should not be used in the treatment of venereal diseases, including syphilis, gonorrhea, yaws, bejel, and pinta.

CONTRAINDICATIONS

A previous hypersensitivity reaction to any penicillin or to procaine is a contraindication.

WARNINGS

WARNING: NOT FOR INTRAVENOUS USE. DO NOT INJECT INTRAVENOUSLY OR ADMIX WITH OTHER INTRAVENOUS SOLUTIONS. THERE HAVE BEEN REPORTS OF INADVERTENT INTRAVENOUS ADMINISTRATION OF PENICILLIN G BENZATHINE WHICH HAS BEEN ASSOCIATED WITH CARDIORESPIRATORY ARREST AND DEATH. Prior to administration of this drug, carefully read the WARNINGS, ADVERSE REACTIONS, and DOSAGE AND ADMINISTRATION sections of the labeling.

The combination of penicillin G benzathine and penicillin G procaine should only be prescribed for the indications listed in this insert.

Anaphylaxis

SERIOUS AND OCCASIONALLY FATAL HYPERSENSITIVITY (ANAPHYLACTIC) REACTIONS HAVE BEEN REPORTED IN PATIENTS ON PENICILLIN THERAPY. THESE REACTIONS ARE MORE LIKELY TO OCCUR IN INDIVIDUALS WITH A HISTORY OF PENICILLIN HYPERSENSITIVITY AND/OR A HISTORY OF SENSITIVITY TO MULTIPLE ALLERGENS. THERE HAVE BEEN REPORTS OF INDIVIDUALS WITH A HISTORY OF PENICILLIN HYPERSENSITIVITY WHO HAVE EXPERIENCED SEVERE REACTIONS WHEN TREATED WITH CEPHALOSPORINS. BEFORE INITIATING THERAPY WITH BICILLIN C-R CAREFUL INQUIRY SHOULD BE MADE CONCERNING PREVIOUS HYPERSENSITIVITY REACTIONS TO PENICILLINS, CEPHALOSPORINS OR OTHER ALLERGENS. IF AN ALLERGIC REACTION OCCURS, BICILLIN C-R SHOULD BE DISCONTINUED AND APPROPRIATE THERAPY INSTITUTED. SERIOUS ANAPHYLACTIC REACTIONS REQUIRE IMMEDIATE EMERGENCY TREATMENT WITH EPINEPHRINE. OXYGEN, INTRAVENOUS STEROIDS AND AIRWAY MANAGEMENT, INCLUDING INTUBATION, SHOULD ALSO BE ADMINISTERED AS INDICATED.

Severe cutaneous adverse reactions (SCAR), such as Stevens-Johnson syndrome (SJS), toxic epidermal necrolysis (TEN), drug reaction with eosinophilia and systemic symptoms (DRESS), and acute generalized exanthematous pustulosis (AGEP) have been reported in patients taking penicillin G (the active moiety in Bicillin C-R). When SCAR is suspected, Bicillin C-R should be discontinued immediately and an alternative treatment should be considered.

Methemoglobinemia

Cases of methemoglobinemia have been reported in association with local anesthetic use. Although all patients are at risk for methemoglobinemia, patients with glucose-6-phosphate dehydrogenase deficiency, congenital or idiopathic methemoglobinemia, cardiac or pulmonary compromise, infants under 6 months of age, and concurrent exposure to oxidizing agents or their metabolites are more susceptible to developing clinical manifestations of the condition. If local anesthetics must be used in these patients, close monitoring for symptoms and signs of methemoglobinemia is recommended.

Signs of methemoglobinemia may occur immediately or may be delayed some hours after exposure, and are characterized by a cyanotic skin discoloration and/or abnormal coloration of the blood. Methemoglobin levels may continue to rise; therefore, immediate treatment is required to avert more serious central nervous system (CNS) and cardiovascular adverse effects, including seizures, coma, arrhythmias, and death. Discontinue Bicillin C-R and any other oxidizing agents. Depending on the severity of the signs and symptoms, patients may respond to supportive care, i.e., oxygen therapy, hydration. A more severe clinical presentation may require treatment with methylene blue, exchange transfusion, or hyperbaric oxygen.

Clostridioides difficile associated diarrhea

Clostridioides difficile associated with diarrhea (CDAD) has been reported with use of nearly all antibacterial agents, including Bicillin C-R, and may range in severity from mild diarrhea to fatal colitis. Treatment with antibacterial agents alters the normal flora of the colon leading to overgrowth of C. difficile.

C. difficile produces toxins A and B which contribute to the development of CDAD. Hypertoxin producing strains of C. difficile cause increased morbidity and mortality, as these infections can be refractory to antimicrobial therapy and may require colectomy. CDAD must be considered in all patients who present with diarrhea following antibiotic use. Careful medical history is necessary since CDAD has been reported to occur over two months after the administration of antibacterial agents.

If CDAD is suspected or confirmed, ongoing antibiotic use not directed against C. difficile may need to be discontinued. Appropriate fluid and electrolyte management, protein supplementation, antibiotic treatment of C. difficile, and surgical evaluation should be instituted as clinically indicated.

Method of Administration

Do not inject into or near an artery or nerve. See administration instructions below.

Injection into or near a nerve may result in permanent neurological damage.

Inadvertent intravascular administration, including inadvertent direct intra-arterial injection or injection immediately adjacent to arteries, of Bicillin C-R and other penicillin preparations has resulted in severe neurovascular damage, including transverse myelitis with permanent paralysis, gangrene requiring amputation of digits and more proximal portions of extremities, and necrosis and sloughing at and surrounding the injection site consistent with the diagnosis of Nicolau syndrome. Such severe effects have been reported following injections into the buttock, thigh, and deltoid areas. Other serious complications of suspected intravascular administration which have been reported include immediate pallor, mottling, or cyanosis of the extremity both distal and proximal to the injection site, followed by bleb formation; severe edema requiring anterior and/or posterior compartment fasciotomy in the lower extremity. The above-described severe effects and complications have most often occurred in infants and small children. Prompt consultation with an appropriate specialist is indicated if any evidence of compromise of the blood supply occurs at, proximal to, or distal to the site of injection.^1–9 (See PRECAUTIONS, and DOSAGE AND ADMINISTRATION sections.)

FOR DEEP INTRAMUSCULAR INJECTION ONLY. There have been reports of inadvertent intravenous administration of penicillin G benzathine which has been associated with cardiorespiratory arrest and death. Therefore, do not inject intravenously or admix with other intravenous solutions. (See DOSAGE AND ADMINISTRATION section.)

Administer by DEEP INTRAMUSCULAR INJECTION ONLY in the upper, outer quadrant of the buttock (dorsogluteal) or the ventrogluteal site. Quadriceps femoris fibrosis and atrophy have been reported following repeated intramuscular injections of penicillin preparations into the anterolateral thigh. Because of these adverse effects and the vascularity of this region, administration in the anterolateral thigh is not recommended.

PRECAUTIONS

General

Prescribing Bicillin C-R in the absence of a proven or strongly suspected bacterial infection or a prophylactic indication is unlikely to provide benefit to the patient and increases the risk of a development of drug-resistant bacteria.

Penicillin should be used with caution in individuals with histories of significant allergies and/or asthma.

Care should be taken to avoid intravenous or intra-arterial administration, or injection into or near major peripheral nerves or blood vessels, since such injections may produce neurovascular damage. (See WARNINGS, and DOSAGE AND ADMINISTRATION sections.)

A small percentage of patients are sensitive to procaine. If there is a history of sensitivity, make the usual test: Inject intradermally 0.1 mL of a 1 to 2 percent procaine solution. Development of an erythema, wheal, flare, or eruption indicates procaine sensitivity. Sensitivity should be treated by the usual methods, including barbiturates, and procaine penicillin preparations should not be used. Antihistamines appear beneficial in treatment of procaine reactions.

The use of antibiotics may result in overgrowth of nonsusceptible organisms. Constant observation of the patient is essential. If new infections due to bacteria or fungi appear during therapy, the drug should be discontinued and appropriate measures taken.

Whenever allergic reactions occur, penicillin should be withdrawn unless, in the opinion of the physician, the condition being treated is life-threatening and amenable only to penicillin therapy.

In prolonged therapy with penicillin, and particularly with high-dosage schedules, periodic evaluation of the renal and hematopoietic systems is recommended.

Information for Patients

Inform patients that use of local anesthetics may cause methemoglobinemia, a serious condition that must be treated promptly. Advise patients or caregivers to seek immediate medical attention if they or someone in their care experience the following signs or symptoms: pale, gray, or blue colored skin (cyanosis); headache; rapid heart rate; shortness of breath; lightheadedness; or fatigue.

Diarrhea is a common problem caused by antibiotics which usually ends when the antibiotic is discontinued. Sometimes after starting treatment with antibiotics, patients can develop watery and bloody stools (with or without stomach cramps and fever) even as late as two months after having taken the last dose of the antibiotic. If this occurs, patients should contact their physician as soon as possible.

Patients should be counseled that antibacterial drugs including Bicillin C-R should only be used to treat bacterial infections. They do not treat viral infections (e.g., the common cold). When Bicillin C-R is prescribed to treat a bacterial infection, patients should be told that although it is common to feel better early in the course of therapy, the medication should be taken exactly as directed. Skipping doses or not completing the full course of therapy may (1) decrease the effectiveness of the immediate treatment and (2) increase the likelihood that bacteria will develop resistance and will not be treatable by Bicillin C-R or other antibacterial drugs in the future.

Laboratory Tests

In streptococcal infections, therapy must be sufficient to eliminate the organism; otherwise, the sequelae of streptococcal disease may occur. Cultures should be taken following completion of treatment to determine whether streptococci have been eradicated.

Drug Interactions

Tetracycline, a bacteriostatic antibiotic, may antagonize the bactericidal effect of penicillin, and concurrent use of these drugs should be avoided.

Concurrent administration of penicillin and probenecid increases and prolongs serum penicillin levels by decreasing the apparent volume of distribution and slowing the rate of excretion by competitively inhibiting renal tubular secretion of penicillin.

Patients who are administered local anesthetics are at increased risk of developing methemoglobinemia when concurrently exposed to the following drugs, which could include other local anesthetics:

Examples of Drugs Associated with Methemoglobinemia:
Class | Examples
Nitrates/Nitrites | nitroglycerin, nitroprusside, nitric oxide, nitrous oxide
Local anesthetics | articaine, benzocaine, bupivacaine, lidocaine, mepivacaine, prilocaine, procaine, ropivacaine, tetracaine
Antineoplastic agents | cyclophosphamide, flutamide, hydroxyurea, ifosfamide, rasburicase
Antibiotics | dapsone, nitrofurantoin, para-aminosalicylic acid, sulfonamides
Antimalarials | chloroquine, primaquine
Anticonvulsants | phenobarbital, sodium valproate
Other drugs | acetaminophen, metoclopramide, quinine, sulfasalazine

Pregnancy

Teratogenic effects

Reproduction studies performed in the mouse, rat, and rabbit have revealed no evidence of impaired fertility or harm to the fetus due to penicillin G. Human experience with the penicillins during pregnancy has not shown any positive evidence of adverse effects on the fetus. There are, however, no adequate and well-controlled studies in pregnant women showing conclusively that harmful effects of these drugs on the fetus can be excluded. Because animal reproduction studies are not always predictive of human response, this drug should be used during pregnancy only if clearly needed.

Nursing Mothers

Soluble penicillin G (the hydrolysate of penicillin G benzathine) is excreted in breast milk. Caution should be exercised when penicillin G benzathine and penicillin G procaine are administered to a nursing woman.

Carcinogenesis, Mutagenesis, Impairment of Fertility

No long-term animal studies have been conducted with these drugs.

Pediatric Use

(See INDICATIONS AND USAGE and DOSAGE AND ADMINISTRATION sections.)

Geriatric use

Clinical studies of penicillin G benzathine and penicillin G procaine did not include sufficient numbers of subjects aged 65 and over to determine whether they respond differently from younger subjects. Other reported clinical experience has not identified differences in responses between the elderly and younger patients. In general, dose selection for an elderly patient should be cautious, usually starting at the low end of the dosing range, reflecting the greater frequency of decreased hepatic, renal, or cardiac function, and of concomitant disease or other drug therapy. This drug is known to be substantially excreted by the kidney, and the risk of toxic reactions to this drug may be greater in patients with impaired renal function (See CLINICAL PHARMACOLOGY.) Because elderly patients are more likely to have decreased renal function, care should be taken in dose selection, and it may be useful to monitor renal function.

ADVERSE REACTIONS

As with other penicillins, untoward reactions of the sensitivity phenomena are likely to occur, particularly in individuals who have previously demonstrated hypersensitivity to penicillins or in those with a history of allergy, asthma, hay fever, or urticaria.

The following adverse reactions have been reported with Bicillin C-R during post-marketing experience:

Skin and Appendages: Stevens-Johnson syndrome (SJS) and drug reaction with eosinophilia and systemic symptoms (DRESS) (See WARNINGS.)

The following have been reported with parenteral penicillin G (the active moiety in Bicillin C-R):

General: Hypersensitivity reactions including the following: skin eruptions (maculopapular to exfoliative dermatitis), urticaria, laryngeal edema, fever, eosinophilia; other serum sickness-like reactions (including chills, fever, edema, arthralgia, and prostration); and anaphylaxis including shock and death: severe cutaneous adverse reactions (SCAR), such as toxic epidermal necrolysis (TEN) and acute generalized exanthematous pustulosis (AGEP) (See WARNINGS.) Note: Urticaria, other skin rashes, and serum sickness-like reactions may be controlled with antihistamines and, if necessary, systemic corticosteroids. Whenever such reactions occur, penicillin G should be discontinued unless, in the opinion of the physician, the condition being treated is life-threatening and amenable only to therapy with penicillin G. Serious anaphylactic reactions require immediate emergency treatment with epinephrine. Oxygen, intravenous steroids, and airway management, including intubation, should also be administered as indicated.

Gastrointestinal: Pseudomembranous colitis. Onset of pseudomembranous colitis symptoms may occur during or after antibacterial treatment. (See WARNINGS section.)

Hematologic: Hemolytic anemia, leukopenia, thrombocytopenia.

Neurologic: Neuropathy.

Urogenital: Nephropathy.

The following adverse events have been temporally associated with parenteral administrations of penicillin G benzathine (a component of Bicillin C-R):

Body as a Whole: Hypersensitivity reactions including allergic vasculitis, pruritis, fatigue, asthenia, and pain; aggravation of existing disorder; headache, Nicolau syndrome.

Cardiovascular: Cardiac arrest; hypotension; tachycardia; palpitations; pulmonary hypertension; pulmonary embolism; vasodilation; vasovagal reaction; cerebrovascular accident; syncope.

Gastrointestinal: Nausea, vomiting; blood in stool; intestinal necrosis.

Hemic and Lymphatic: Lymphadenopathy.

Immune System Disorders: Acute myocardial ischemia with or without myocardial infarction may occur as part of an allergic reaction (Kounis syndrome).

Injection Site: Injection site reactions including pain, inflammation, lump, abscess, necrosis, edema, hemorrhage, cellulitis, hypersensitivity, atrophy, ecchymosis, and skin ulcer. Neurovascular reactions including warmth, vasospasm, pallor, mottling, gangrene, numbness of the extremities, cyanosis of the extremities, and neurovascular damage.

Metabolic: Elevated BUN, creatinine, and SGOT.

Musculoskeletal: Joint disorder, periostitis; exacerbation of arthritis; myoglobinuria; rhabdomyolysis.

Nervous System: Nervousness; tremors; dizziness; somnolence; confusion; anxiety; euphoria; transverse myelitis; seizures; coma. A syndrome manifested by a variety of CNS symptoms such as severe agitation with confusion, visual and auditory hallucinations, and a fear of impending death (Hoigne's syndrome), has been reported after administration of penicillin G procaine and, less commonly, after injection of the combination of penicillin G benzathine and penicillin G procaine. Other symptoms associated with this syndrome, such as psychosis, seizures, dizziness, tinnitus, cyanosis, palpitations, tachycardia, and/or abnormal perception in taste, also may occur.

Respiratory: Hypoxia; apnea; dyspnea.

Skin: Diaphoresis.

Special Senses: Blurred vision; blindness.

Urogenital: Neurogenic bladder; hematuria; proteinuria; renal failure; impotence; priapism.

OVERDOSAGE

Penicillin in overdosage has the potential to cause neuromuscular hyperirritability or convulsive seizures.

DOSAGE AND ADMINISTRATION

Streptococcal Infections Group A

Infections of the upper-respiratory tract, skin and soft-tissue infections, scarlet fever, and erysipelas.

The following doses are recommended:

Adults and pediatric patients over 60 lbs. in weight: 2,400,000 units.

Pediatric patients from 30 to 60 lbs.: 900,000 units to 1,200,000 units.

Pediatric patients under 30 lbs.: 600,000 units.

NOTE: Treatment with the recommended dosage is usually given at a single session using multiple IM sites when indicated. An alternative dosage schedule may be used, giving one-half (1/2) the total dose on day 1 and one-half (1/2) on day 3. This will also insure the penicillinemia required over a 10-day period; however, this alternate schedule should be used only when the physician can be assured of the patient's cooperation.

Pneumococcal Infections (except pneumococcal meningitis)

600,000 units in pediatric patients and 1,200,000 units in adults, repeated every 2 or 3 days until the temperature is normal for 48 hours. Other forms of penicillin may be necessary for severe cases.

Method of Administration

Bicillin C-R is intended for Intramuscular Injection ONLY. Do not inject into or near an artery or nerve, or intravenously or admix with other intravenous solutions. (See WARNINGS section).

Administer by DEEP INTRAMUSCULAR INJECTION in the upper, outer quadrant of the buttock (dorsogluteal) or the ventrogluteal site. In neonates, infants and small children, the midlateral aspect of the thigh may be preferable. Administration in the anterolateral thigh is not recommended due to the adverse effects observed (see WARNINGS section), and vascularity of this region. When doses are repeated, vary the injection site.

Because of the high concentration of suspended material in this product, the needle may be blocked if the injection is not made at a slow, steady rate.

Parenteral drug products should be inspected visually for particulate matter and discoloration prior to administration whenever solution and container permit.

HOW SUPPLIED

Bicillin C-R (penicillin G benzathine and penicillin G procaine injectable suspension) is supplied in packages of 10 disposable syringes as follows:

2 mL size, containing 1,200,000 units per syringe (21 gauge, thin-wall 1-inch needle for pediatric use), NDC 60793-601-10.

2 mL size, containing 1,200,000 units per syringe (21 gauge, thin-wall 1-1/2-inch needle), NDC 60793-600-10.

STORAGE AND HANDLING

Store in a refrigerator, 2º to 8º (36º to 46ºF).

Keep from freezing.

REFERENCES

1. SHAW, E.: Transverse myelitis from injection of penicillin. Am. J. Dis. Child., 111:548, 1966.
2. KNOWLES, J.: Accidental intra-arterial injection of penicillin. Am. J. Dis. Child., 111:552, 1966.
3. DARBY, C. et al: Ischemia following an intragluteal injection of benzathine-procaine penicillin G mixture in a one-year-old boy. Clin. Pediatrics, 12:485, 1973.
4. BROWN, L. & NELSON, A.: Postinfectious intravascular thrombosis with gangrene. Arch. Surg., 94:652, 1967.
5. BORENSTINE, J.: Transverse myelitis and penicillin (Correspondence). Am. J. Dis. Child., 112:166, 1966.
6. ATKINSON, J.: Transverse myelopathy secondary to penicillin injection. J. Pediatrics, 75:867, 1969.
7. TALBERT, J. et al: Gangrene of the foot following intramuscular injection in the lateral thigh: A case report with recommendations for prevention. J. Pediatrics, 70:110, 1967.
8. FISHER, T.: Medicolegal affairs. Canad. Med. Assoc. J., 112:395, 1975.
9. SCHANZER, H. et al: Accidental intra-arterial injection of penicillin G. JAMA, 242:1289, 1979.

LAB-0635-18.0
Revised: 09/2023

PRINCIPAL DISPLAY PANEL - 2 mL Syringe Label - 601

NDC 60793-601-02

BICILLIN® C-R
(600,000 units penicillin G benzathine and
600,000 units penicillin G procaine injectable
suspension)
1,200,000 units per 2 mL
Not for the Treatment of Syphilis
FOR DEEP INTRAMUSCULAR INJECTION ONLY
WARNING: FATAL IF GIVEN BY OTHER ROUTES

Distributed by
Pfizer Inc
New York, NY 10017

PRINCIPAL DISPLAY PANEL - 2 mL Syringe Package - 601

NDC 60793-601-10
Contains 10 of NDC 60793-601-02

Ten Syringes (2 mL size)

Bicillin® C-R
(penicillin G benzathine and penicillin G procaine
injectable suspension)

1,200,000 units per 2 mL

FOR PEDIATRIC USE

FOR DEEP INTRAMUSCULAR INJECTION ONLY

WARNING: FATAL IF GIVEN BY OTHER ROUTES
BEFORE INJECTING, SEE PACKAGE INSERT FOR ADMINISTRATION INSTRUCTIONS.

NOT FOR THE TREATMENT OF SYPHILIS

Pfizer Injectables

Rx only

PRINCIPAL DISPLAY PANEL - 2 mL Syringe Label - 600

NDC 60793-600-02

BICILLIN® C-R
(penicillin G benzathine and penicillin G
procaine injectable suspension in equal
portions)
1,200,000 units per 2 mL
Not for the Treatment of Syphilis
FOR DEEP INTRAMUSCULAR INJECTION ONLY
WARNING: FATAL IF GIVEN BY OTHER ROUTES

Distributed by
Pfizer Inc
New York, NY 10017

PRINCIPAL DISPLAY PANEL - 2 mL Syringe Package - 600

NDC 60793-600-10
Contains 10 of NDC 60793-600-02

Ten Syringes (2 mL size)

Bicillin® C-R
(penicillin G benzathine and penicillin G procaine
injectable suspension)

1,200,000 units per 2 mL

FOR DEEP INTRAMUSCULAR INJECTION ONLY

WARNING: FATAL IF GIVEN BY OTHER ROUTES
BEFORE INJECTING, SEE PACKAGE INSERT FOR ADMINISTRATION INSTRUCTIONS.

NOT FOR THE TREATMENT OF SYPHILIS

Pfizer Injectables

Rx only